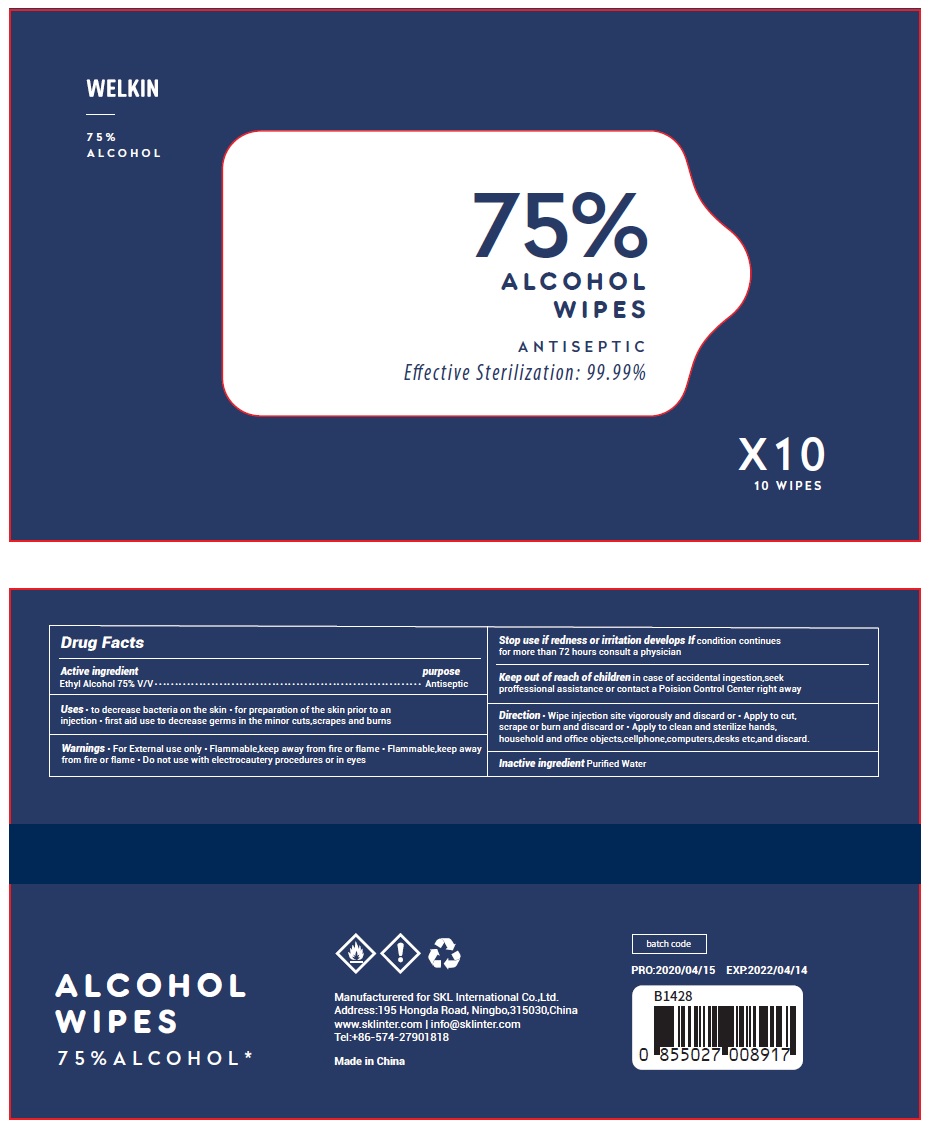 DRUG LABEL: WELKIN 75% Alcohol Wipes
NDC: 74542-003 | Form: CLOTH
Manufacturer: Ningbo SKL International Co.,Ltd.
Category: otc | Type: HUMAN OTC DRUG LABEL
Date: 20200610

ACTIVE INGREDIENTS: ALCOHOL 0.75 mL/1 1
INACTIVE INGREDIENTS: WATER

Active Ingredient

Ethyl Alcohol 75% v/v.

Purpose

Antiseptic

Use

To decrease bacteria on the skin

To preparation of the skin prior to an injection

First aid use to decrease germs in the minor cuts, scrapes and burns.

Warnings

For external use only
Flammable, keep away from fire or flame
Do not use with electrocautery procedures or in eyes

Stop use

If redness or irritation develops
If condition continues for more than 72 hours consult a physician

Keep out of reach of children. If swallowed, get medical help or contact a Poison Control Center right away.

Directions

- Place enough product on hands to cover all surfaces. Rub hands together until dry.
- Supervise children under 6 years of age when using this product to avoid swallowing.

Inactive ingredients

Purified water